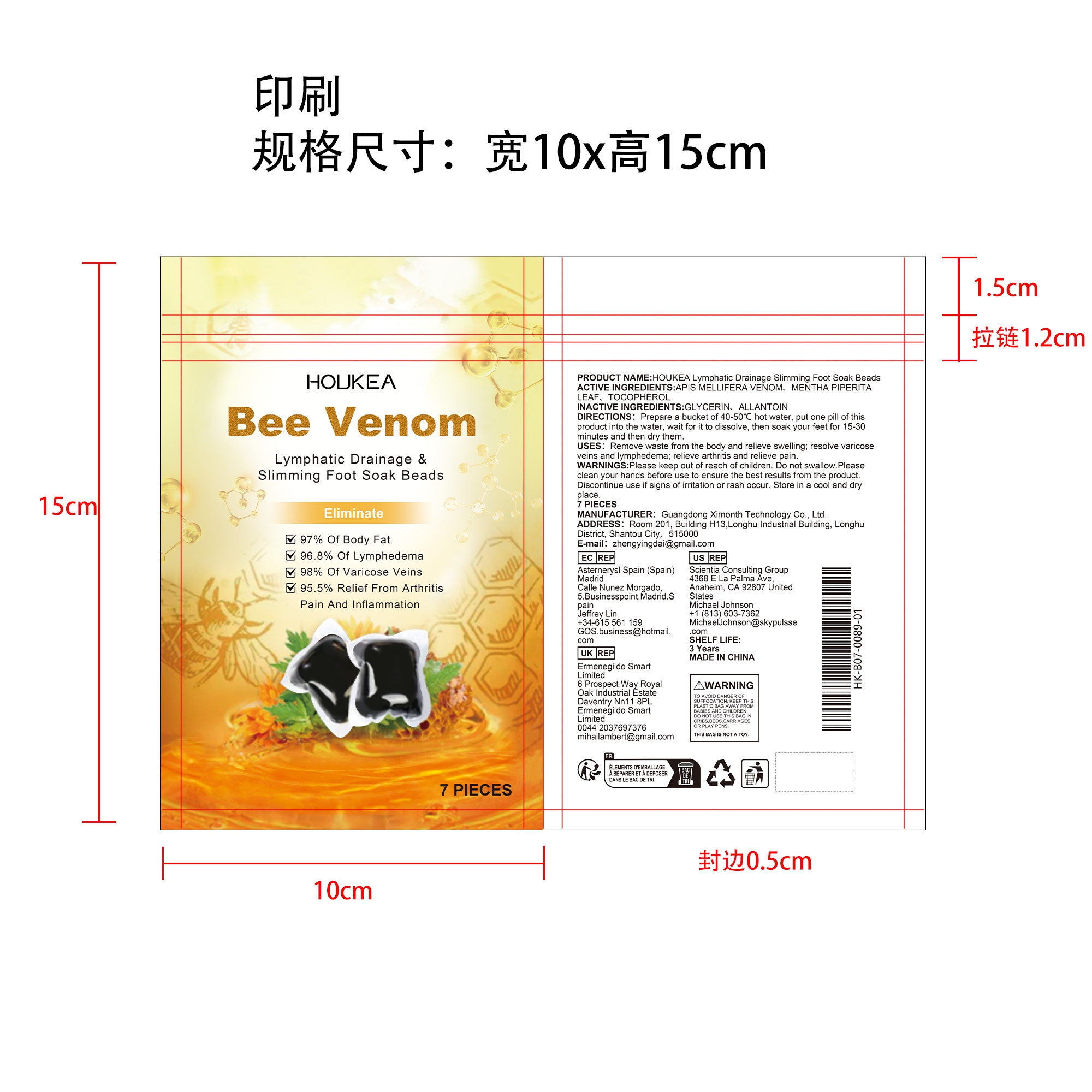 DRUG LABEL: HOUKEA Lymphatic Drainage Slimming Foot Soak Beads
NDC: 84660-094 | Form: LIQUID
Manufacturer: Guangdong Ximonth Technology Co., Ltd.
Category: otc | Type: HUMAN OTC DRUG LABEL
Date: 20241029

ACTIVE INGREDIENTS: APIS MELLIFERA VENOM 2.1 g/7 g; MENTHA PIPERITA LEAF 0.7 g/7 g; TOCOPHEROL 1.05 g/7 g
INACTIVE INGREDIENTS: GLYCERIN 1.05 g/7 g; ALLANTOIN 2.1 g/7 g

ACTIVE INGREDIENTS

APIS MELLIFERA VENOM,MENTHA PIPERITA LEAF,TOCOPHEROL

PURPOSE

Remove waste from the body and relieve swelling; resolve varicoseveins and lymphedema; relieve arthritis and relieve pain.

USES

Prepare a bucket of 40-50℃ hot water, put one pill of this product into the water, wait for it to dissolve, then soak your feet for 15-30 minutes and then dry them.

WARNINGS

Please keep out of reach of children. Do not swallow.Please clean your hands before use to ensure the best results from the product. Discontinue use if signs of irritation or rash occur. Store in a cool and dry place.

STOP USE

Discontinue use if signs of irritation or rash occur.

DO NOT USE

Discontinue use if signs of irritation or rash occur.

KEEP OUT OF REACH OF CHILDREN

Please keep out of reach of children. Do not swallow

STORAGE AND HANDLING

Store in a cool and dry place.

INACTIVE INGREDIENT

GLYCERIN、ALLANTOIN